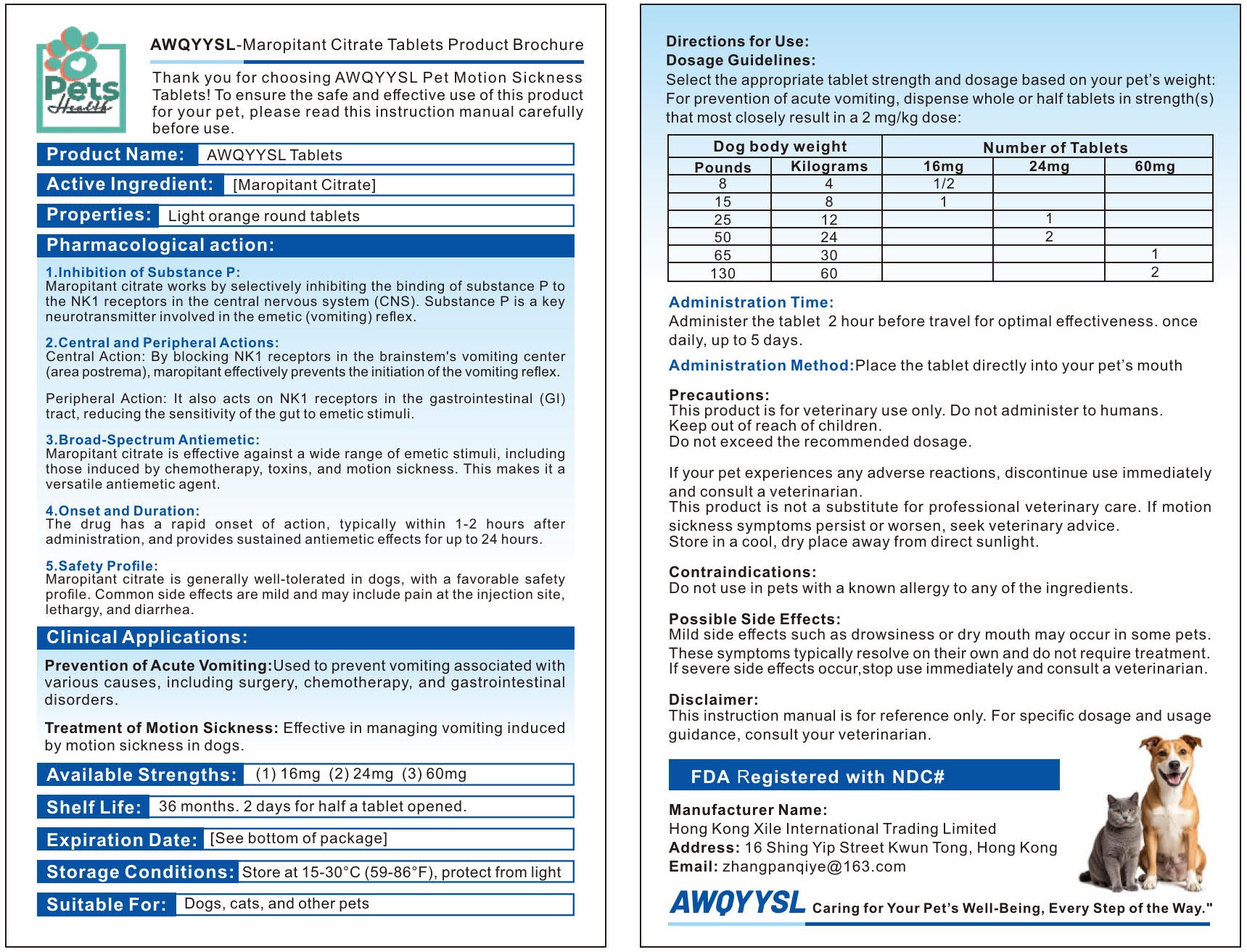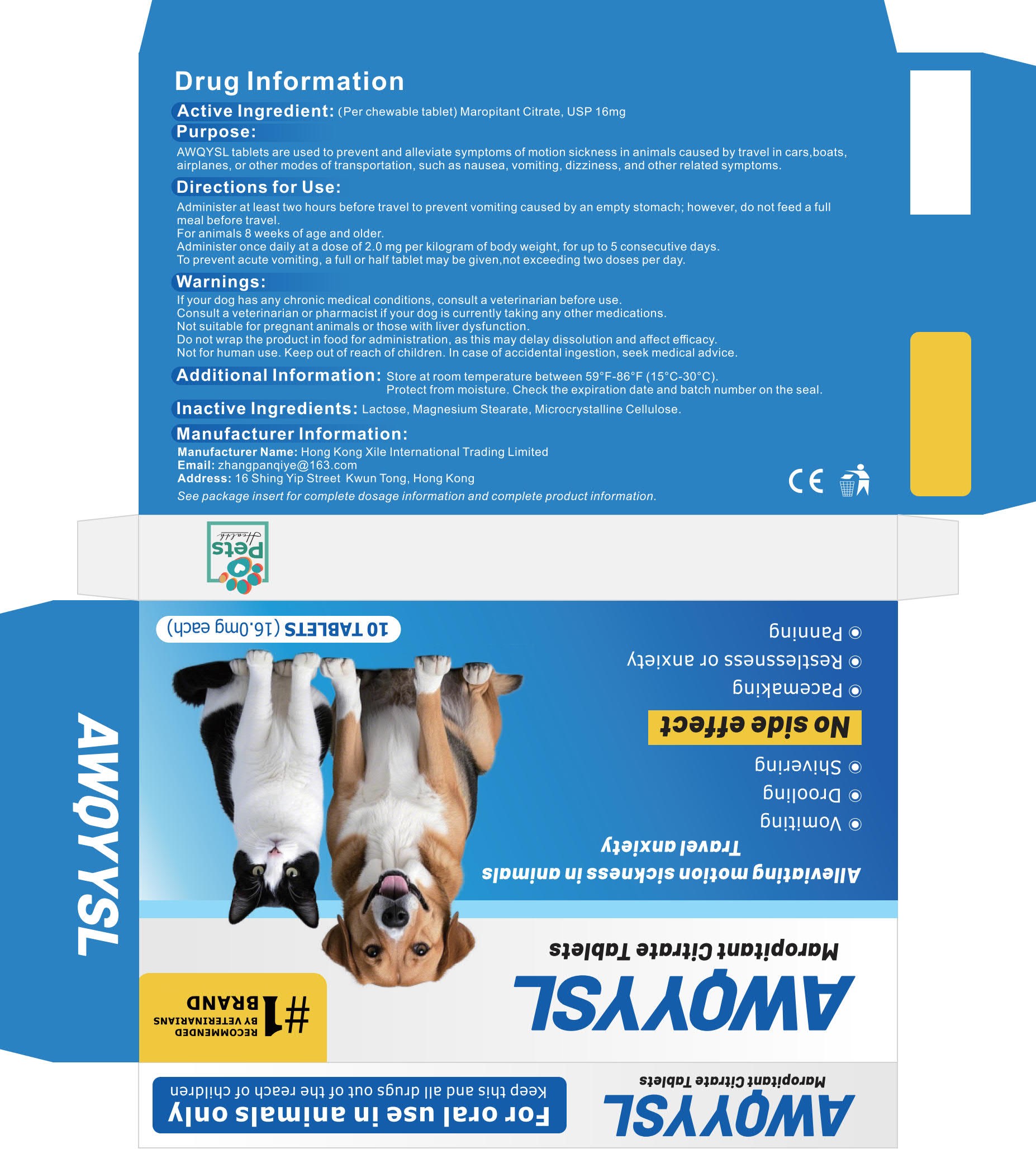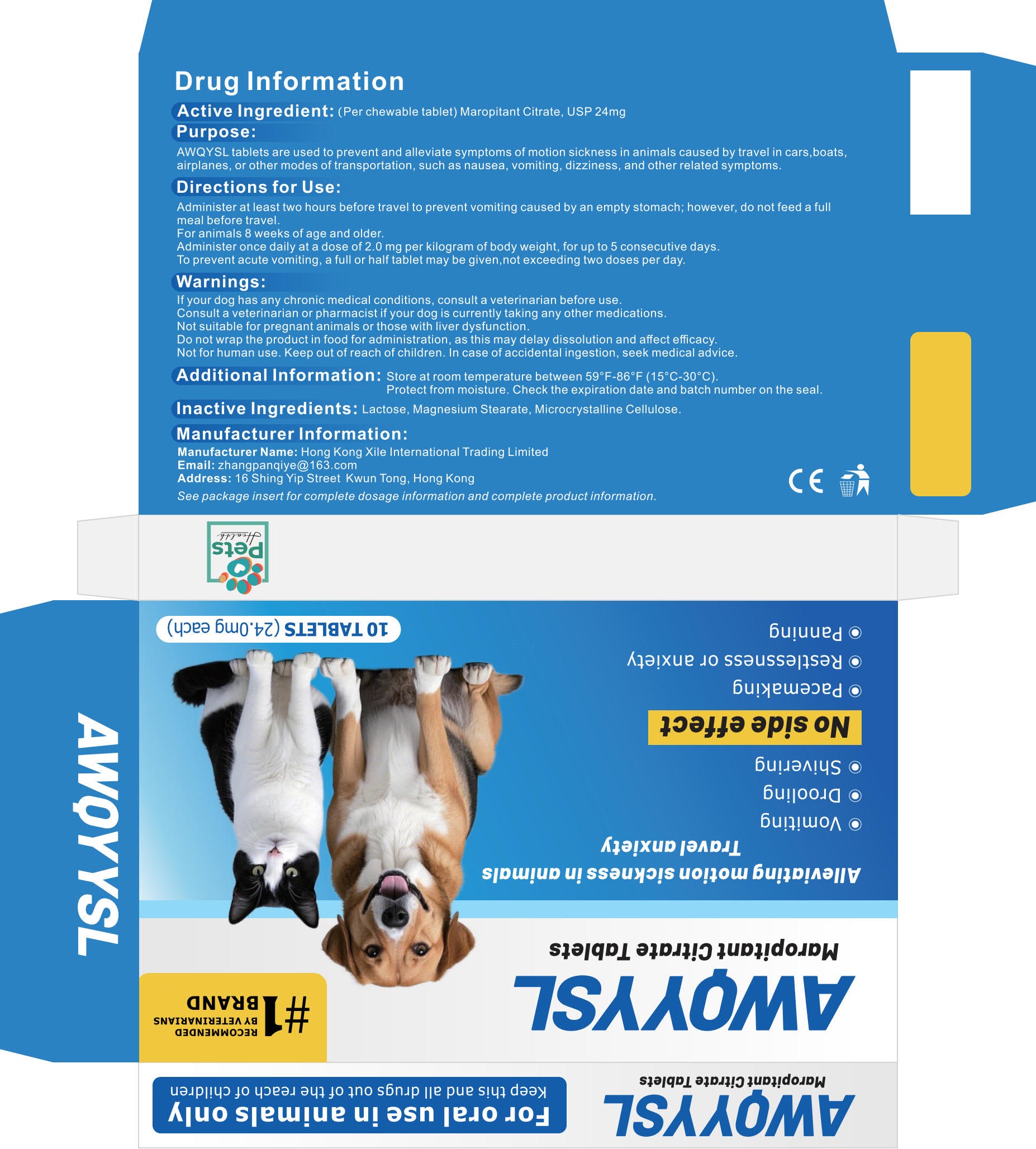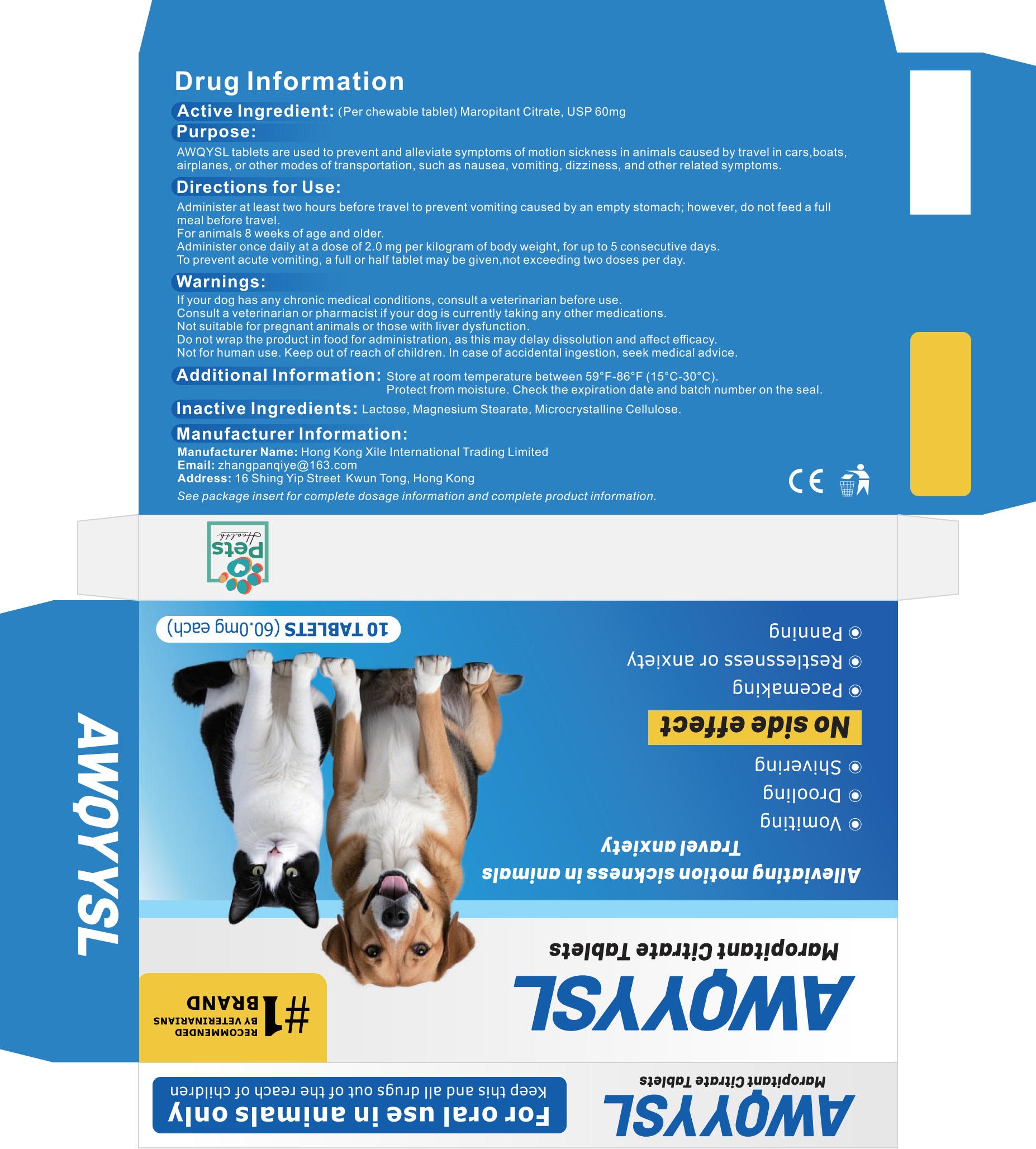 DRUG LABEL: AWQYYSL Pet Motion Sickness
NDC: 85209-101 | Form: TABLET
Manufacturer: Hong Kong Xile International Trading Limited
Category: animal | Type: OTC ANIMAL DRUG LABEL
Date: 20250626

ACTIVE INGREDIENTS: Maropitant Citrate 10 mg/100 mg
INACTIVE INGREDIENTS: Lactose; Magnesium stearate; Microcrystalline Cellulose

Xile, AWQYYSL Pet Motion Sickness Tablets, 16 / 24 / 60mg *10 tablets each box

WARNINGS AND PRECAUTIONS

This product is for veterinary use only. Do not administer to humans.
Keep out of reach of children.
Do not exceed the recommended dosage.

INDICATIONS AND USAGE

Prevention of Acute Vomiting: Used to prevent vomiting associated with various causes, including surgery, chemotherapy, and gastrointestinal disorders.
Treatment of Motion Sickness: Eﬀective in managing vomiting induced by motion sickness in dogs.
Suitable for dogs, cats, and other pets.

DOSAGE AND ADMINISTRATION

Select the appropriate tablet strength and dosage based on your pet’s weight: For prevention of acute vomiting, dispense whole or half tablets in strength(s) that most closely result in a 2 mg/kg dose.

Administration Time:
Administer the tablet 2 hour before travel for optimal eﬀectiveness. Once
daily, up to 5 days.
Administration Method:
Place the tablet directly into your pet's mouth.

ACTIVE INGREDIENT

Maropitant Citrate, 10% w/w

INACTIVE INGREDIENT

Lactose
Magnesium Stearate
Microcrystalline Cellulose

ADVERSE REACTIONS

Mild side eﬀects such as drowsiness or dry mouth may occur in some pets.
These symptoms typically resolve on their own and do not require treatment.
If severe side eﬀects occur, stop use immediately and consult a veterinarian.

Keep out of reach of children.

STORAGE AND HANDLING

Store at 15-30°C (59-86°F), protect from light.

Do not use in pets with a known allergy to any of the ingredients.